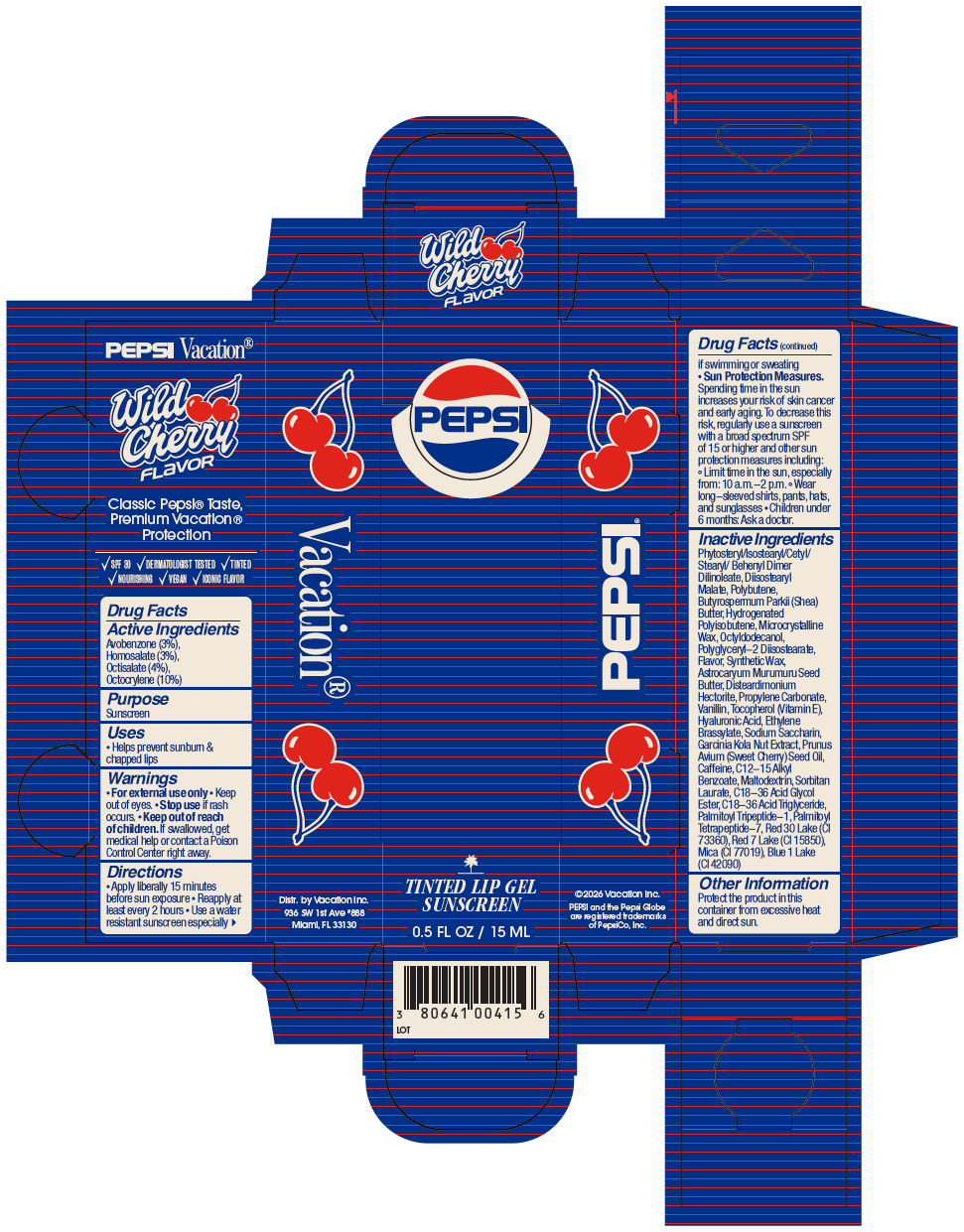 DRUG LABEL: Vacation Lip Balm
NDC: 80641-520 | Form: GEL
Manufacturer: Vacation INC.
Category: otc | Type: HUMAN OTC DRUG LABEL
Date: 20260127

ACTIVE INGREDIENTS: Avobenzone 3 g/100 mL; Homosalate 3 g/100 mL; Octisalate 4 g/100 mL; Octocrylene 10 g/100 mL
INACTIVE INGREDIENTS: Phytosteryl/Isostearyl/Cetyl/Stearyl/Behenyl Dimer Dilinoleate; Diisostearyl Malate; POLYBUTENE (1400 MW); SHEA BUTTER; Microcrystalline Wax; ETHYLHEXYL COCOATE; SYNTHETIC WAX (1200 MW); Disteardimonium Hectorite; Astrocaryum Murumuru Seed Butter; Vanillin; Propylene Carbonate; HYALURONATE SODIUM; D&C RED NO. 30; Ethylene Brassylate; SACCHARIN SODIUM ANHYDROUS; .ALPHA.-TOCOPHEROL; Caffeine; SWEET CHERRY SEED OIL; ALKYL (C12-15) BENZOATE; GARCINIA KOLA SEED; Mica; Maltodextrin; SORBITAN MONOLAURATE; C18-36 Acid Triglyceride; Palmitoyl Tripeptide-1; Palmitoyl Tetrapeptide-7

Vacation® Lip Gel Balm

Drug Facts

Active Ingredients

Avobenzone (3%), Homosalate (3%), Octisalate (4%), Octocrylene (10%)

Purpose

Sunscreen

Uses

- Helps prevent sunburn & chapped lips

Warnings

- For external use only
- Keep out of eyes.

- Stop use if rash occurs.

- Keep out of reach of children. If swallowed, get medical help or contact a Poison Control Center right away.

Directions

- Apply liberally 15 minutes before sun exposure
- Reapply at least every 2 hours
- Use a water resistant sunscreen especially if swimming or sweating
- Sun Protection Measures. Spending time in the sun increases your risk of skin cancer and early aging. To decrease this risk, regularly use a sunscreen with a broad spectrum SPF of 15 or higher and other sun protection measures including:
  - Limit time in the sun, especially from: 10 a.m.-2 p.m.
  - Wear long-sleeved shirts, pants, hats, and sunglasses
- Children under 6 months: Ask a doctor.

Inactive Ingredients

Phytosteryl/Isostearyl/Cetyl/ Stearyl/ Behenyl Dimer Dilinoleate, Diisostearyl Malate, Polybutene, Butyrospermum Parkii (Shea) Butter, Hydrogenated Polyisobutene, Microcrystalline Wax, Octyldodecanol, Polyglyceryl-2 Diisostearate, Flavor, Synthetic Wax, Astrocaryum Murumuru Seed Butter, Disteardimonium Hectorite, Propylene Carbonate, Vanillin, Tocopherol (Vitamin E), Hyaluronic Acid, Ethylene Brassylate, Sodium Saccharin, Garcinia Kola Nut Extract, Prunus Avium (Sweet Cherry) Seed Oil, Caffeine, C12-15 Alkyl Benzoate, Maltodextrin, Sorbitan Laurate, C18-36 Acid Glycol Ester, C18-36 Acid Triglyceride, Palmitoyl Tripeptide-1, Palmitoyl Tetrapeptide-7, Red 30 Lake (CI 73360), Red 7 Lake (CI 15850), Mica (CI 77019), Blue 1 Lake (CI 42090)

Other Information

Protect the product in this container from excessive heat and direct sun.

Distr. by Vacation Inc.
936 SW 1st Ave #888
Miami, FL 33130

PRINCIPAL DISPLAY PANEL - 15 ML Tube Carton

PEPSI

TINTED LIP GEL
SUNSCREEN

0.5 FL OZ / 15 ML